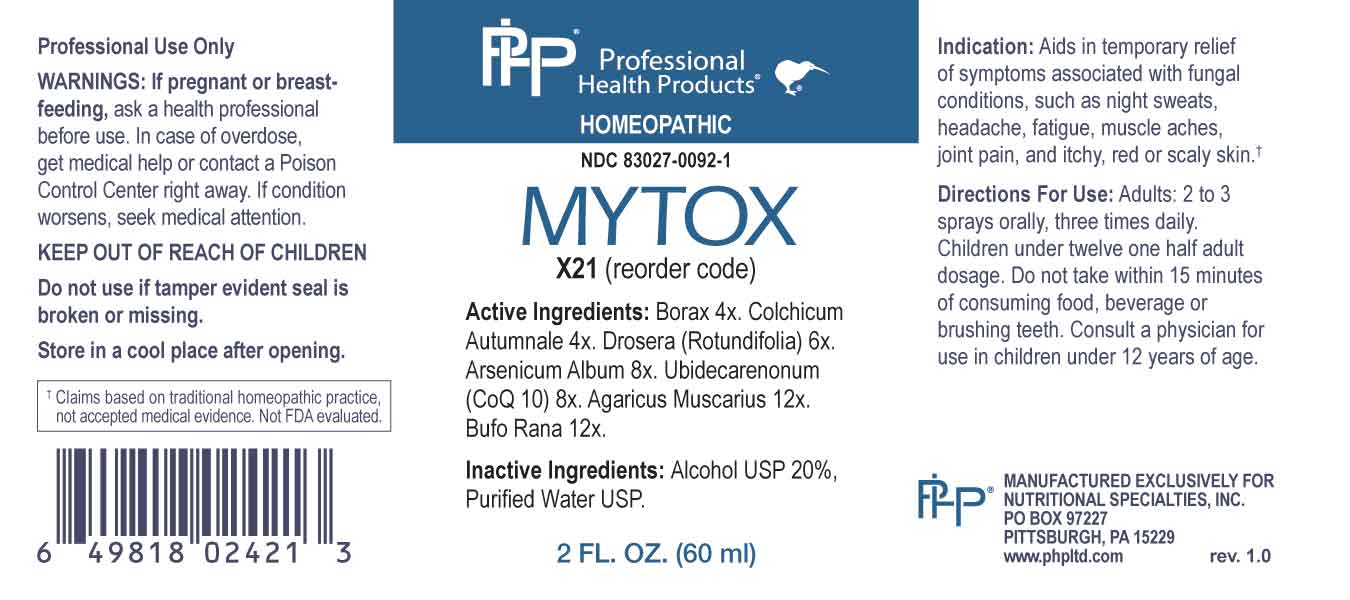 DRUG LABEL: Mytox
NDC: 83027-0092 | Form: SPRAY
Manufacturer: Nutritional Specialties, Inc.
Category: homeopathic | Type: HUMAN OTC DRUG LABEL
Date: 20230802

ACTIVE INGREDIENTS: SODIUM BORATE 4 [hp_X]/1 mL; COLCHICUM AUTUMNALE BULB 4 [hp_X]/1 mL; DROSERA ROTUNDIFOLIA WHOLE 6 [hp_X]/1 mL; ARSENIC TRIOXIDE 8 [hp_X]/1 mL; UBIDECARENONE 8 [hp_X]/1 mL; AMANITA MUSCARIA FRUITING BODY 12 [hp_X]/1 mL; BUFO BUFO CUTANEOUS GLAND 12 [hp_X]/1 mL
INACTIVE INGREDIENTS: WATER; ALCOHOL

DRUG FACTS:

ACTIVE INGREDIENTS:

Borax 4X, Colchicum Autumnale 4X, Drosera (Rotundifolia) 6X, Arsenicum Album 8X, Ubidecarenonum (CoQ 10) 8X, Agaricus Muscarius 12X, Bufo Rana 12X.

PURPOSE:

Aids in temporary relief of symptoms associated with fungal conditions, such as night sweats, headache, fatigue, muscle aches, joint pain, and itchy, red or scaly skin†

†Claims based on traditional homeopathic practice, not accepted medical evidence. Not FDA evaluated.

WARNINGS:

Professional Use Only

If pregnant or breast-feeding, ask a health professional before use.

In case of overdose, get medical help or contact a Poison Control Center right away.

If condition worsens, seek medical attention.

KEEP OUT OF REACH OF CHILDREN

Do not use if tamper evident seal is broken or missing.

Store in a cool place after opening

KEEP OUT OF REACH OF CHILDREN:

In case of overdose, get medical help or contact a Poison Control Center right away.

DIRECTIONS:

Adults: 2 to 3 sprays orally, three times daily. Children under twelve one half adult dosage. Do not take within 15 minutes of consuming food, beverage or brushing teeth. Consult a physician for use in children under 12 years of age.

INDICATIONS:

Aids in temporary relief of symptoms associated with fungal conditions, such as night sweats, headache, fatigue, muscle aches, joint pain, and itchy, red or scaly skin†

†Claims based on traditional homeopathic practice, not accepted medical evidence. Not FDA evaluated.

INACTIVE INGREDIENTS:

Alcohol USP 20%, Purified Water USP.

QUESTIONS:

MANUFACTURED EXCLUSIVELY FOR

NUTRITIONAL SPECIALTIES, INC.

PO BOX 97227

PITTSBURG, PA 15229

www.phpltd.com

PACKAGE LABEL DISPLAY:

Professional

Health Products

HOMEOPATHIC

NDC 83027-0092-1

MYTOX

2 FL. OZ (60 ml)